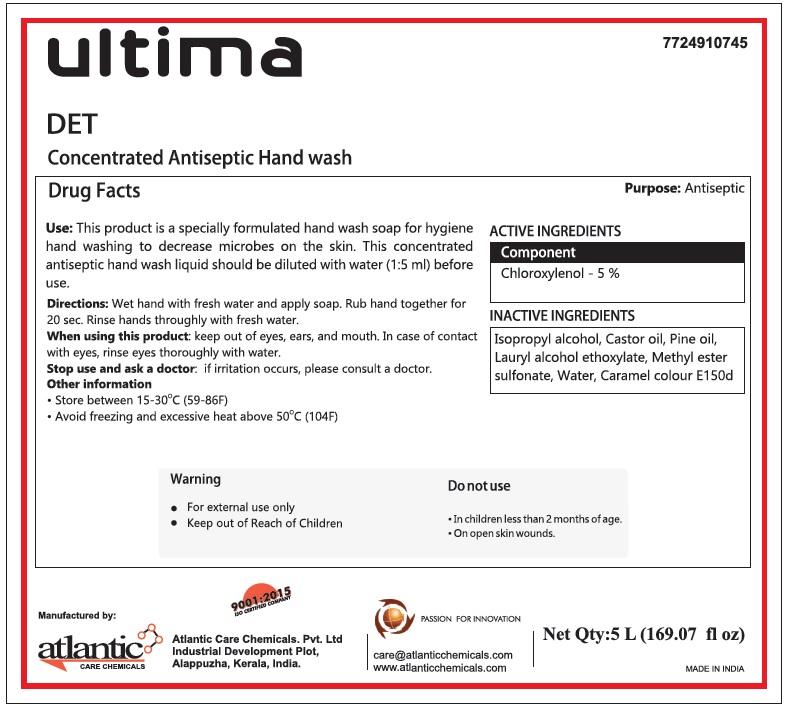 DRUG LABEL: Ultima DET Antiseptic
NDC: 77249-107 | Form: LIQUID
Manufacturer: ATLANTIC CARE CHEMICALS PRIVATE LIMITED
Category: otc | Type: HUMAN OTC DRUG LABEL
Date: 20200521

ACTIVE INGREDIENTS: CHLOROXYLENOL 50 g/1 L
INACTIVE INGREDIENTS: ISOPROPYL ALCOHOL; CASTOR OIL; WHITE PINE OIL; LAURYL ALCOHOL; S-METHYL METHANETHIOSULFONATE; WATER; CARAMEL

ultima DET Concentrated Antiseptic Hand wash

Purpose: Antiseptic

ACTIVE INGREDIENTS

Component

Chloroxylenol - 5 %

INACTIVE INGREDIENTS

Isopropyl alcohol, Castor oil, Pine oil, Lauryl alcohol ethoxylate, Methyl ester sulfonate, Water, Caramel colour E150d

INDICATIONS AND USAGE

Use: This product is a specially formulated hand wash soap for hygiene hand washing to decrease microbes on the skin. This concentrated antiseptic hand wash liquid should be diluted with water (1:5 ml) before use.

DOSAGE AND ADMINISTRATION

Directions: Wet hand with fresh water and apply soap. Rub hand together for 20 sec. Rinse hands thoroughly with fresh water.

When using this product: keep out of eyes, ears, and mouth. In case of contact with eyes, rinse eyes thoroughly with water.

Stop use and ask a doctor: if irritation occurs, please consult a doctor.

Do not use

• In children less than 2 months of age.

• On open skin wounds.

Warning

• For external use only

• Keep out of Reach of Children

Other information

• Store between 15-30°C (59-86F)

• Avoid freezing and excessive heat above 50°C (104F)

Manufactured by:
Atlantic Care Chemicals. Pvt. Ltd
Industrial Development Plot,
Alappuzha, Kerala, India.

9001:2015

ISO CERTIFIED COMPANY

PASSION FOR INNOVATION

care@atlanticchemicals.com
www.atlanticchemicals.com

MADE IN INDIA